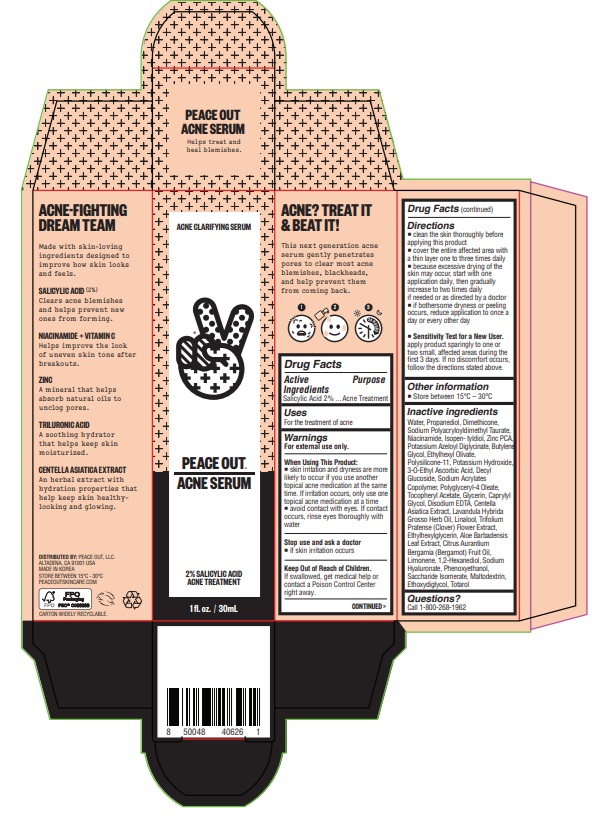 DRUG LABEL: Peace Out Acne Serum
NDC: 71494-102 | Form: LOTION
Manufacturer: Peace Out LLC.
Category: otc | Type: HUMAN OTC DRUG LABEL
Date: 20260114

ACTIVE INGREDIENTS: SALICYLIC ACID 20 mg/1 mL
INACTIVE INGREDIENTS: WATER; PROPANEDIOL; DIMETHICONE; NIACINAMIDE; ISOPENTYLDIOL; SODIUM POLYACRYLOYLDIMETHYL TAURATE; ZINC PIDOLATE; POTASSIUM AZELOYL DIGLYCINATE; ETHYLHEXYL OLIVATE; BUTYLENE GLYCOL; POTASSIUM HYDROXIDE; DIMETHICONE/VINYL DIMETHICONE CROSSPOLYMER (SOFT PARTICLE); 3-O-ETHYL ASCORBIC ACID; .ALPHA.-TOCOPHEROL ACETATE; GLYCERIN; CAPRYLYL GLYCOL; EDETATE DISODIUM ANHYDROUS; CENTELLA ASIATICA WHOLE; LAVANDIN OIL; TRIFOLIUM PRATENSE FLOWER; ETHYLHEXYLGLYCERIN; ALOE VERA LEAF; BERGAMOT OIL; 1,2-HEXANEDIOL; HYALURONATE SODIUM; PHENOXYETHANOL; SACCHARIDE ISOMERATE; MALTODEXTRIN; DIETHYLENE GLYCOL MONOETHYL ETHER; TOTAROL; POLYGLYCERYL-4 OLEATE; DECYL GLUCOSIDE

Peace Out Acne Serum

Active Ingredients

Salicylic Acid 2%

Purpose

Acne Treatment

Uses

For the treatment of acne

Warnings

For external use only.

When Using This Product

- skin irritation and dryness are more likely to occur if you use another topical acne medication at the same time. If irritation occurs, only use one topical acne medication at a time
- avoid contact with eyes. If contact occurs, rinse eyes thoroughly with water

Stop use and ask a doctor

if skin irriation occurs.

Keep Out of Reach of Children.

If swallowed, get medical help or contact a Poison Control Center right away.

Directions

- Clean the skin thoroughly before applying this product
- Cover the entire affected area with a thin layer one to three times daily
- Because excessive drying of the skin may occur, start with one application daily, then gradually increase to two times daily if needed or as directed by a doctor
- If bothersome dryness or peeling occurs, reduce application to once a day or every other day
- Sensitivity Test for a New User. Apply product sparingly to one or two small affected areas during the first 3 days. If no discomfort occurs, follow the directions stated above.

Other information

- Store between 15C - 30C

Inactive Ingredients

Water, Propanediol, Dimethicone, Sodium Polyacryloyldimethyl Taurate, Niacinamide, Isopentyldiol, Zinc PCA, Potassium Azeloyl Diglycinate, Butylene Glycol, Ethylhexyl Olivate, Polysilicone-11, Potassium Hydroxide, 3-0-Ethyl Ascorbic Acid, Decyl Glucoside, Sodium Acrylates Copolymer, Polyglyceryl-4 Oleate, Tocopheryl Acetate, Glycerin, Caprylyl Glycol, Disodium EDTA, Gentelia Asiatica Extract, Lavandula Hybrida Grosso Herb Oil, Trifolium Pratense (Clover) Flower Extract, Ethylhexylglycerin, Aloe Barbadensis Leaf Extract, Citrus Aurantium Bergamia (Bergamot) Fruit Oil, Limonene, 1,2-Hexanediol, Sodium Hyaluronate, Phenoxyethanol, Saccharide Isomerate, Maltodextrin, Ethoxydiglycol, Totarol

Questions?

Call 1-800-268-1962